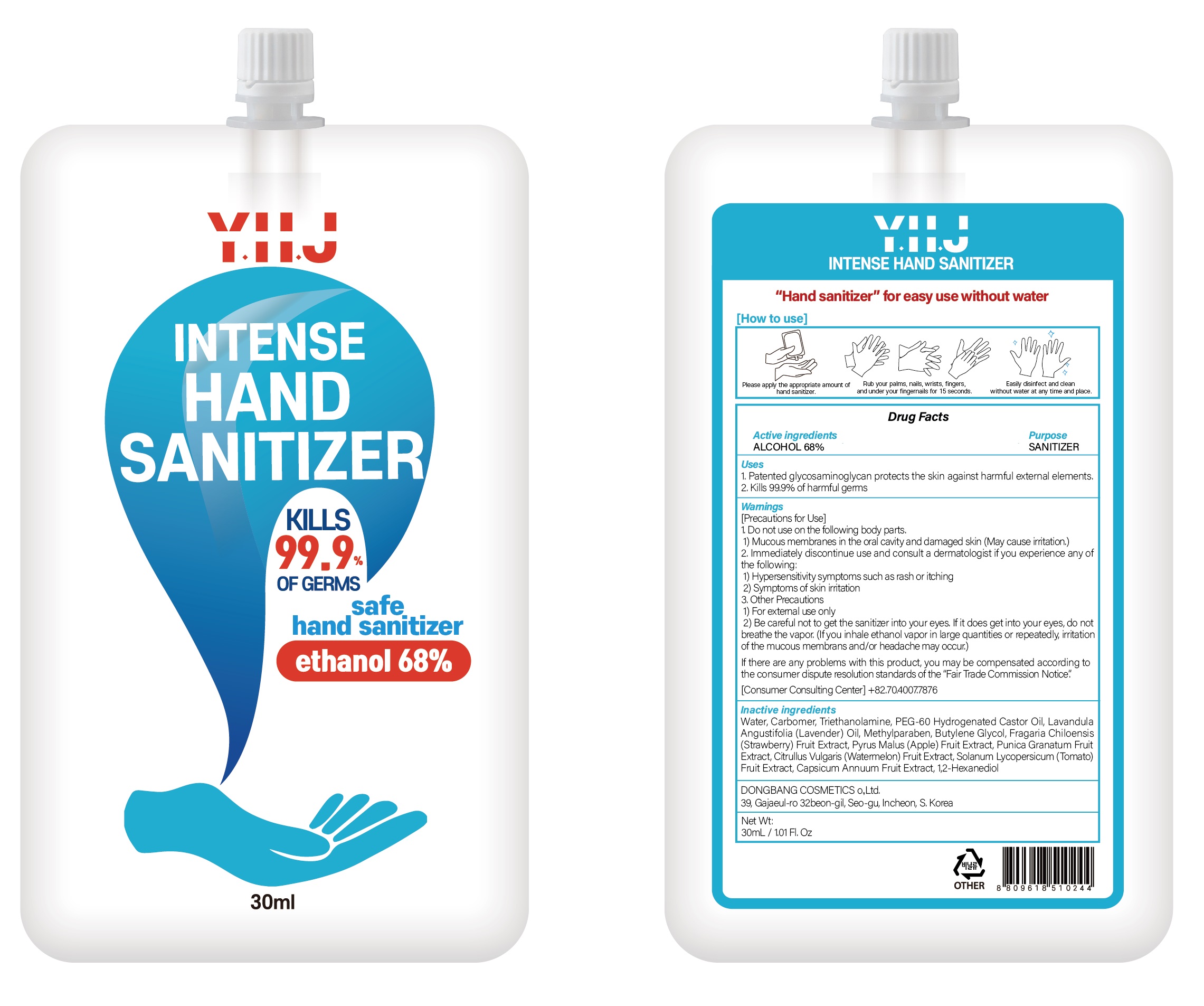 DRUG LABEL: YHJ INTENSE HAND SANITIZER
NDC: 74002-5010 | Form: GEL
Manufacturer: DONGBANGCOSMETICS CO.,LTD
Category: otc | Type: HUMAN OTC DRUG LABEL
Date: 20200408

ACTIVE INGREDIENTS: ALCOHOL 20.4 g/30 mL
INACTIVE INGREDIENTS: Water; CARBOMER HOMOPOLYMER, UNSPECIFIED TYPE; TROLAMINE; PEG-60 Hydrogenated Castor Oil; LAVENDER OIL; Methylparaben; Butylene Glycol

ACTIVE INGREDIENT

Active ingredients: ALCOHOL 68.0%

INACTIVE INGREDIENT

Inactive Ingredients:

Water, Carbomer, Triethanolamine, PEG-60 Hydrogenated Castor Oil, Lavandula Angustifolia (Lavender) Oil, Methylparaben, Butylene Glycol, Fragaria Chiloensis (Strawberry) Fruit Extract, Pyrus Malus (Apple) Fruit Extract, Punica Granatum Fruit Extract, Citrullus Vulgaris (Watermelon) Fruit Extract, Solanum Lycopersicum (Tomato) Fruit Extract, Capsicum Annuum Fruit Extract, 1,2-Hexanediol

PURPOSE

Purpose: SANITIZER

WARNINGS

[Precautions for Use]
1. Do not use on the following body parts.
1) Mucous membranes in the oral cavity and damaged skin (May cause irritation.)
2. Immediately discontinue use and consult a dermatologist if you experience any of the following:
1) Hypersensitivity symptoms such as rash or itching
2) Symptoms of skin irritation
3. Other Precautions
1) For external use only
2) Be careful not to get the sanitizer into your eyes. If it does get into your eyes, do not breathe the vapor. (If you inhale ethanol vapor in large quantities or repeatedly, irritation of the mucous membrans and/or headache may occur.)
If there are any problems with this product, you may be compensated according to the consumer dispute resolution standards of the “Fair Trade Commission Notice”.

KEEP OUT OF REACH OF CHILDREN

Uses

1. Patented glycosaminoglycan protects the skin against harmful external elements.
2. Kills 99.9% of harmful germs

Directions

Take an appropriate amount on your hands and rub thoroughly to dry